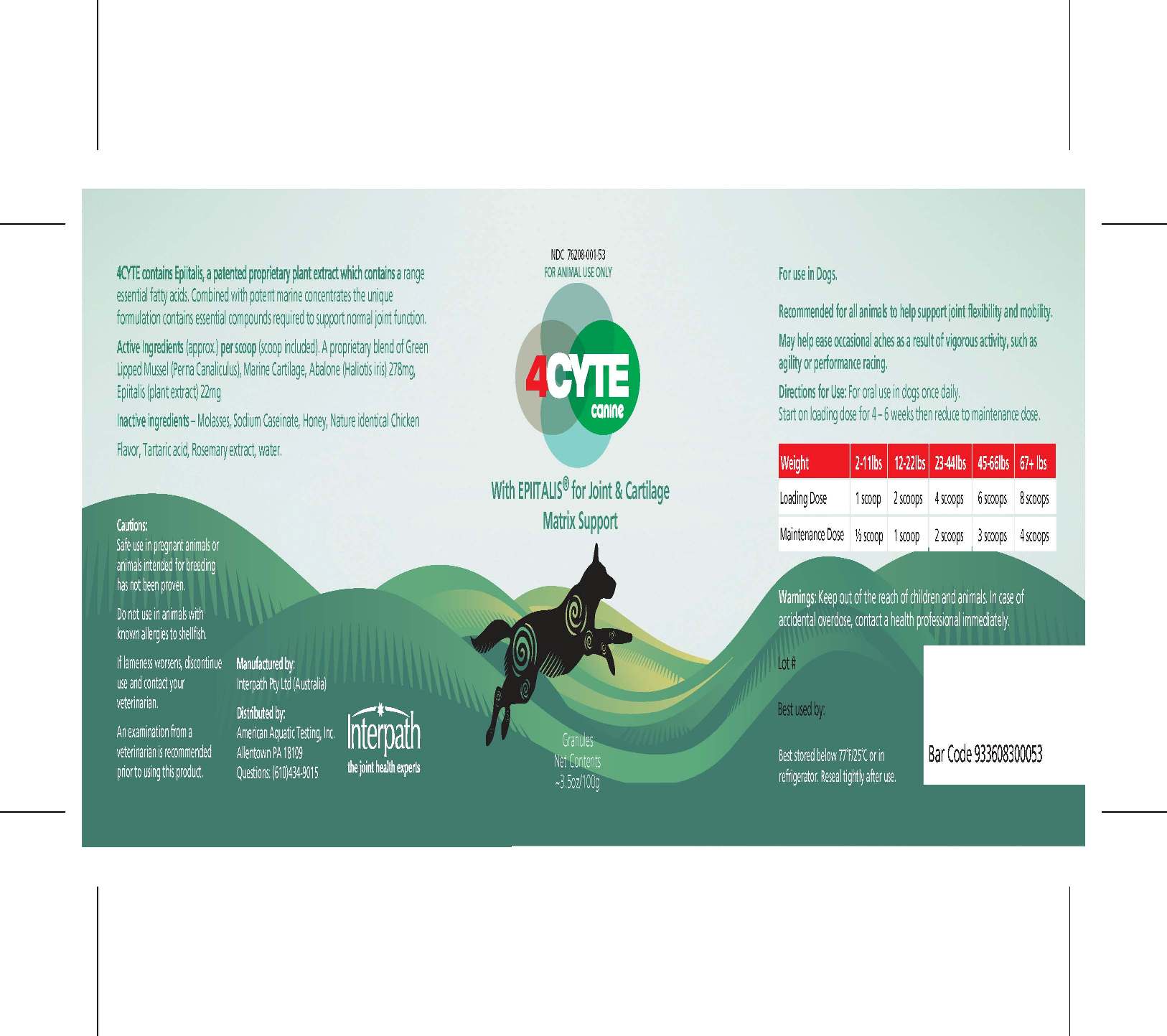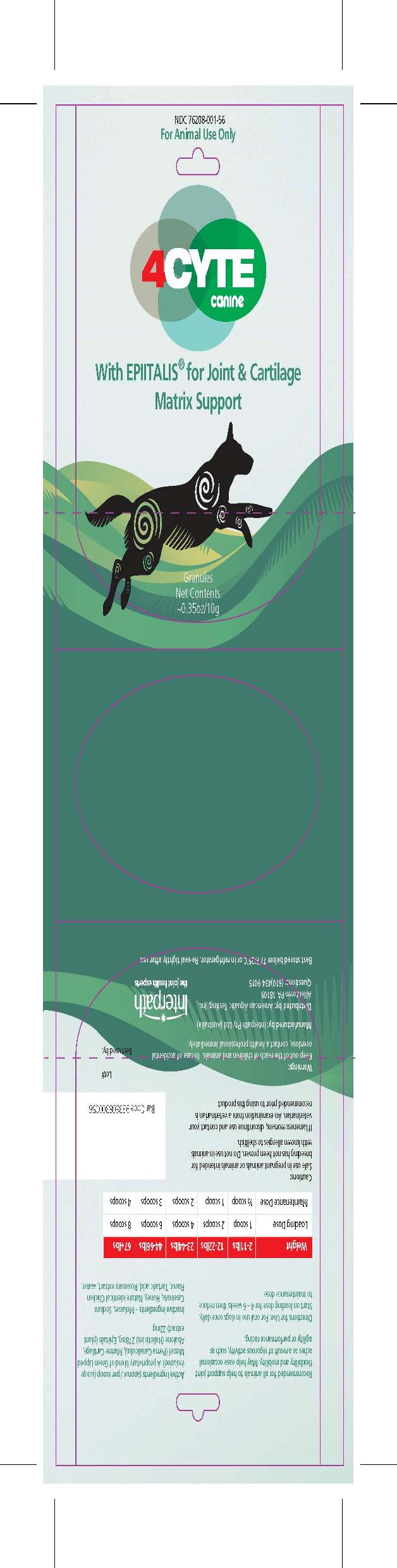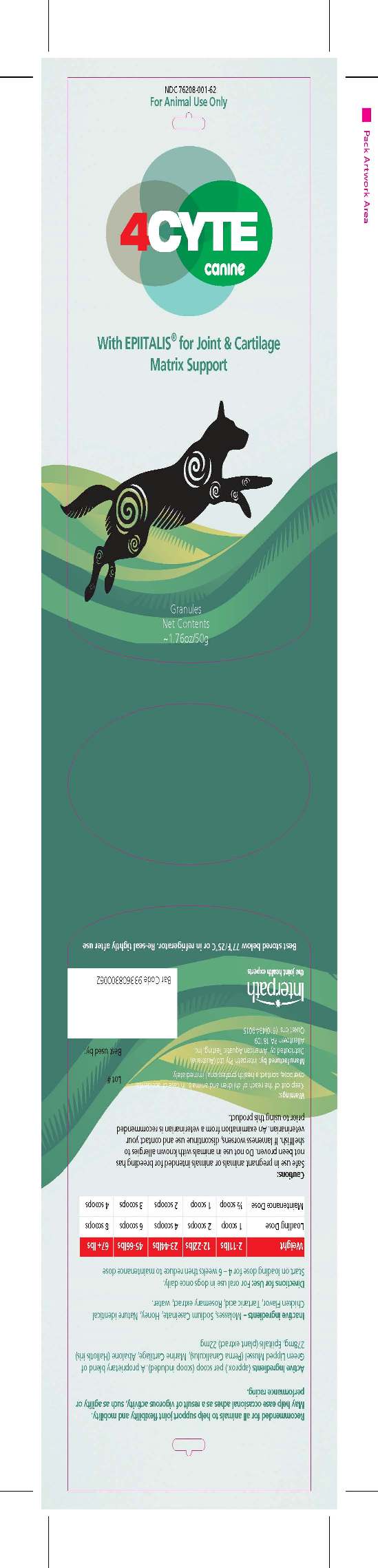 DRUG LABEL: Canine with Epiitalis for Joint and Cartilage Matrix Support
NDC: 76208-001 | Form: GRANULE
Manufacturer: American Aquatic Testing, Inc.
Category: animal | Type: OTC ANIMAL DRUG LABEL
Date: 20110811

ACTIVE INGREDIENTS: NEW ZEALAND GREEN MUSSEL 408 mg/1 g; BLACKFOOT ABALONE 136 mg/1 g; SHARK 136 mg/1 g; PLATYCLADUS ORIENTALIS SEED 54 mg/1 g

4CYTE Canine with Epiitalis for Joint and Cartilage Matrix Support 4CYTE Canine with Epiitalis for Joint and Cartilage Matrix Support

Front Panel

NDC 76208-001-53
For Animal Use Only
4CYTE
CANINE with
EPIITALIS for Joint and
Cartilage Matrix Support
Granules
Net Contents
~3.5oz (100g) bottle

DESCRIPTION

4CYTE contains Epiitalis, a patented proprietary plant extract which
contains a range essential fatty acids. Combined with potent marine
concentrates the unique formulation contains essential compounds required
to support normal joint functio

INDICATIONS AND USAGE

For use in Dogs.
Recommended for all animals to help support joint flexibility and mobility.
May help ease occasional aches as a result of vigorous activity, such as
agility or performance racing.

Active Ingredients (approx.) per scoop (scoop included)
A proprietary blend of Green Lipped Mussel (Perna
Canaliculus),Abalone (Haliotis iris),
Marine Cartilage…………………………………….278mg
Epiitalis (plant extract) ……………………………22mg

DOSAGE AND ADMINISTRATION

Weight 2 – 11lbs 12 -22lbs 23 – 44lbs 45 – 66lbs 67+ lbs
Loading Dose 1 scoop 2 scoops 4 scoops 6 scoops 8 scoops
Maintenance Dose ½ Scoop 1 scoop 2 scoops 3 scoops 4 scoops

WARNINGS AND PRECAUTIONS

Cautions:
Safe use in pregnant animals or animals intended for breeding has not been proven.
Do not use in animals with known allergies to shellfish.
If lameness worsens, discontinue use and contact your veterinarian.
An examination from a veterinarian is recommended prior to using this product.

Warnings:
Keep out of the reach of children and animals. In case of
accidental overdose, contact a
health professional immediately

Manufactured by: Interpath Pty Ltd (Australia)
Distributed by: American Aquatic Testing, Inc.
Allentown PA 18109
Questions: (610)434-9015

PACKAGE LABEL

Canine 100g Bottle

PACKAGE LABEL

Canine 10g USA Pack

PACKAGE LABEL

Canine 50g